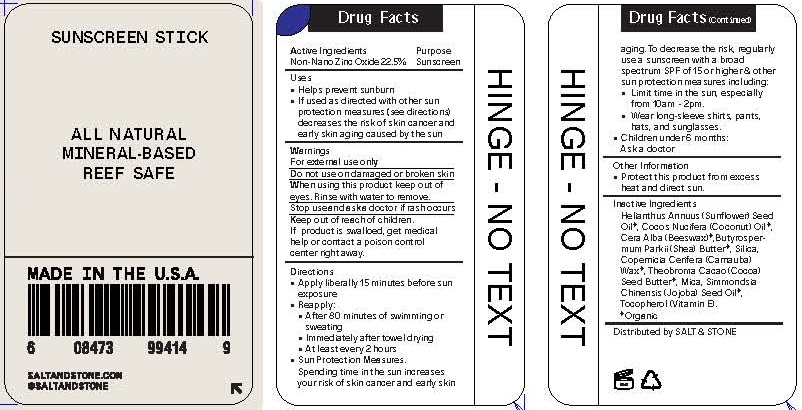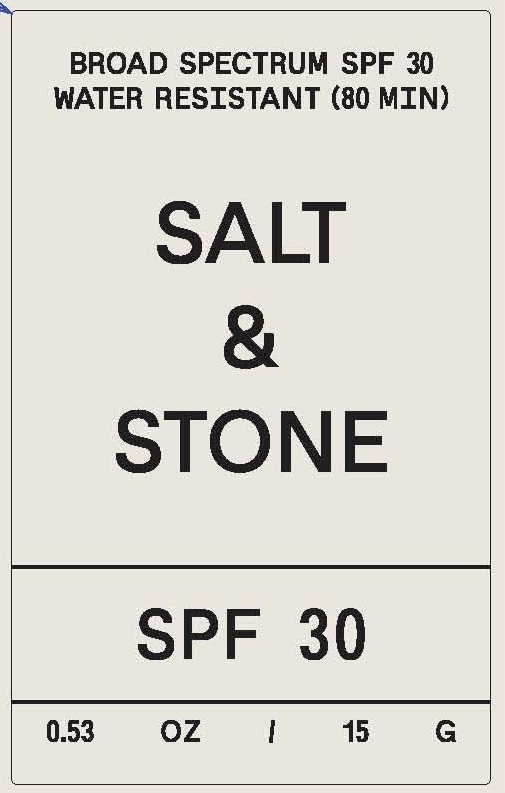 DRUG LABEL: SUNSCREEN
NDC: 71585-107 | Form: STICK
Manufacturer: SALT AND STONE
Category: otc | Type: HUMAN OTC DRUG LABEL
Date: 20190524

ACTIVE INGREDIENTS: ZINC OXIDE 22.5 g/100 g
INACTIVE INGREDIENTS: SHEA BUTTER; YELLOW WAX; COCONUT OIL; CARNAUBA WAX; SUNFLOWER OIL; MICA; SILICON DIOXIDE; JOJOBA OIL; COCOA BUTTER; .ALPHA.-TOCOPHEROL ACETATE; FERROUS OXIDE

MINERAL BASED SALT & STONE PREMIUM SUNSCREEN FACE STICK SPF-30

ACTIVE INGREDIENTS

ZINC OXIDE 22.5%

PURPOSE

SUNSCREEN

USES

- HELPS PREVENT SUNBURN

WARNINGS

FOR EXTERNAL USE ONLY.

DO NOT USE ON DAMAGED OR BROKEN SKIN.

WHEN USING THIS PRODUCT KEEP OUT OF EYES. RINSE WITH WATER TO REMOVE.

STOP USE AND ASK A DOCTOR IF RASH OCCURS.

KEEP OUT OF REACH OF CHILDREN. IF PRODUCT IS SWALLOWED, GET MEDICAL HELP OR CONTACT A POISON CONTROL CENTER RIGHT AWAY.

DIRECTIONS

FOR USE ON CHILDREN LESS THAN 6 MONTHS OF AGE, CONSULT A HEALTH CARE PRACTITIONER. APPLY LIBERALLY/GENEROUSLY (AND EVENLY) 15 MINUTES BEFORE SUN EXPOSURE. REAPPL AFTER 80 MINUTES OF SWIMMING OR SWEATING OR IMMEDIATELY AFTER TOWEL DRYING. REAPPLY AT LEAST EVERY 2 HOURS.

SUN PROTECTION MEASURES. SPENDING TIME IN THE SUN INCREASES YOUR RISK OF SKIN CANCER AND EARLY SKIN AGING. TO DECREASE THIS RISK, REGULARLY USE A SUN SCREEN WITH A BROAD SPECTRUM OF SPF 15 OR HIGHER AND OTHER SUN PROTECTION MEASURES INCLUDING:

- LIMIT TIME IN THE SUN, FROM 10 A.M. - 2 P.M.
- WEAR LONG-SLEEVE SHIRTS, PANTS, HATS, AND SUNGLASSES
- CHILDREN UNDER 6 MONTHS: ASK A DOCTOR

INACTIVE INGREDIENTS

Helianthus Annuus (Sunflower) Seed Oil*, Cocos Nucifera (Coconut) Oil*, Cera Alba (Beeswax)*,Butyrospermum Parkii (Shea) Butter*, Silica, Copernicia Cerifera (Carnauba) Wax*, Theobroma Cacao (Cocoa) Seed Butter*, Mica, Simmondsia Chinensis (Jojoba) Seed Oil*, Tocopherol (Vitamin E).

*Organic

OTHER INFORMATION

- PROTECT THIS PRODUCT FROM EXCESSIVE HEAT AND DIRECT SUN

QUESTIONS OR COMMENTS?

CALL TOLL FREE 1 888 952 4250